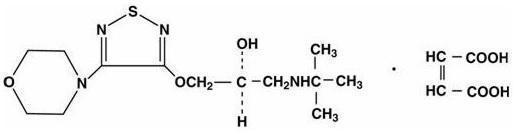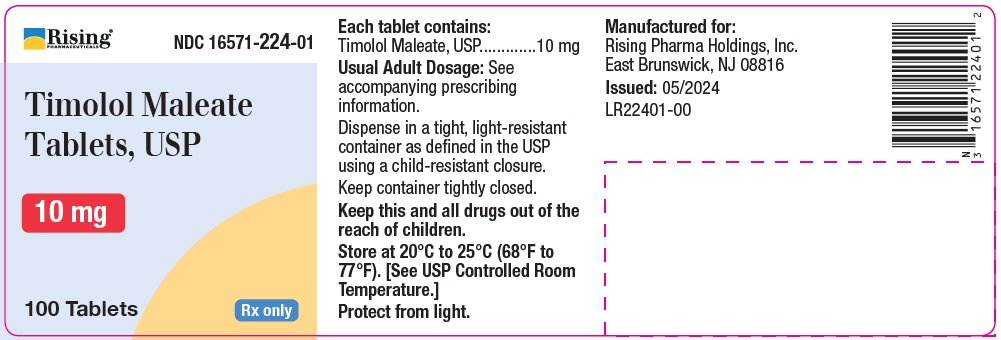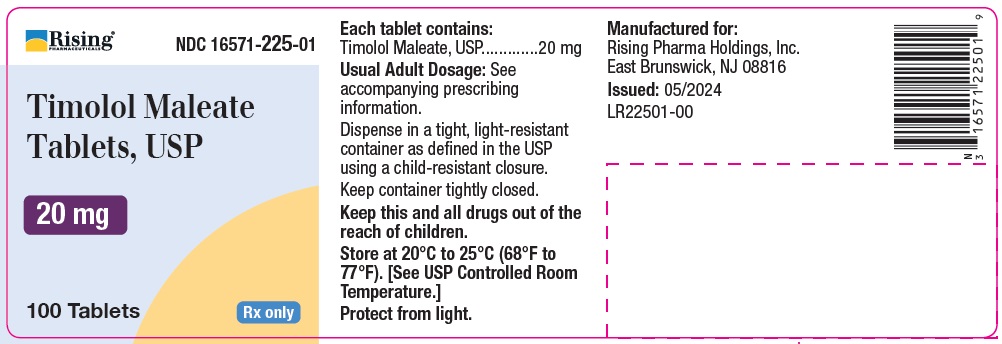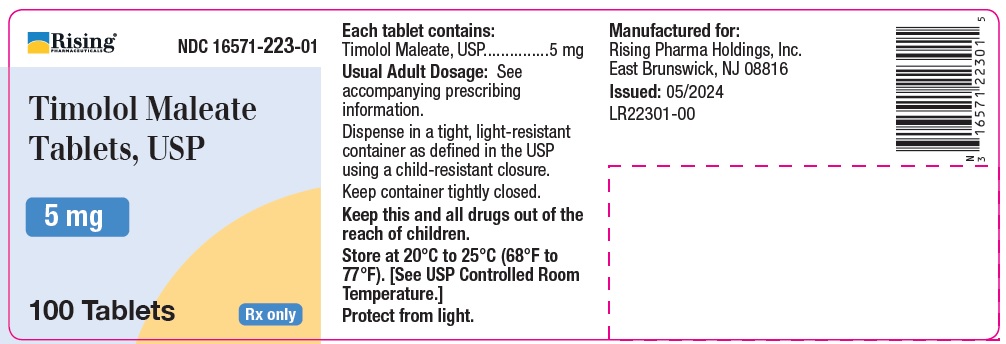 DRUG LABEL: Timolol Maleate
NDC: 16571-223 | Form: TABLET
Manufacturer: Rising Pharma Holdings, Inc.
Category: prescription | Type: HUMAN PRESCRIPTION DRUG LABEL
Date: 20240611

ACTIVE INGREDIENTS: TIMOLOL MALEATE 5 mg/1 1
INACTIVE INGREDIENTS: SILICON DIOXIDE; CROSCARMELLOSE SODIUM; MAGNESIUM STEARATE; CELLULOSE, MICROCRYSTALLINE; STARCH, PREGELATINIZED CORN; SODIUM LAURYL SULFATE

Timolol Maleate

DESCRIPTION

Timolol maleate is a nonselective beta-adrenergic receptor blocking agent. The chemical name for timolol maleate is (S)-1-[(1,1-dimethylethyl)amino]-3-[[4-(4-morpholinyl)-1,2,5-thiadiazol-3-yl]oxy]-2-propanol (Z)-2-butenedioate (1:1) salt. It possesses an asymmetric carbon atom in its structure and is provided as the levo isomer. Its molecular formula is C13H24N4O3S•C4H4O4and its structural formula is:

Timolol maleate has a molecular weight of 432.50. It is a white, odorless, crystalline powder which is soluble in water, methanol, and alcohol.

Timolol maleate is supplied as tablets containing 5 mg, 10 mg and 20 mg timolol maleate for oral administration. Inactive ingredients are: colloidal silicon dioxide, croscarmellose sodium, magnesium stearate, microcrystalline cellulose, pregelatinized maize starch, sodium lauryl sulfate.

CLINICAL PHARMACOLOGY

Timolol maleate is a beta1 and beta2 (nonselective) adrenergic receptor blocking agent that does not have significant intrinsic sympathomimetic, direct myocardial depressant, or local anesthetic activity.

Pharmacodynamics

Clinical pharmacology studies have confirmed the beta-adrenergic blocking activity as shown by (1) changes in resting heart rate and response of heart rate to changes in posture; (2) inhibition of isoproterenol-induced tachycardia; (3) alteration of the response to the Valsalva maneuver and amyl nitrite administration; and (4) reduction of heart rate and blood pressure changes on exercise.

Timolol decreases the positive chronotropic, positive inotropic, bronchodilator, and vasodilator responses caused by beta-adrenergic receptor agonists. The magnitude of this decreased response is proportional to the existing sympathetic tone and the concentration of timolol at receptor sites.

In normal volunteers, the reduction in heart rate response to a standard exercise was dose dependent over the test range of 0.5 to 20 mg, with a peak reduction at 2 hours of approximately 30% at higher doses.

Beta-adrenergic receptor blockade reduces cardiac output in both healthy subjects and patients with heart disease. In patients with severe impairment of myocardial function beta-adrenergic receptor blockade may inhibit the stimulatory effect of the sympathetic nervous system necessary to maintain adequate cardiac function.

Beta-adrenergic receptor blockade in the bronchi and bronchioles results in increased airway resistance from unopposed parasympathetic activity. Such an effect in patients with asthma or other bronchospastic conditions is potentially dangerous.

Clinical studies indicate that timolol maleate at a dosage of 20 to 60 mg/day reduces blood pressure without causing postural hypotension in most patients with essential hypertension. Administration of timolol to patients with hypertension results initially in a decrease in cardiac output, little immediate change in blood pressure, and an increase in calculated peripheral resistance. With continued administration of timolol, blood pressure decreases within a few days, cardiac output usually remains reduced, and peripheral resistance falls toward pretreatment levels. Plasma volume may decrease or remain unchanged during therapy with timolol. In the majority of patients with hypertension timolol also decreases plasma renin activity. Dosage adjustment to achieve optimal antihypertensive effect may require a few weeks. When therapy with timolol is discontinued, the blood pressure tends to return to pretreatment levels gradually. In most patients the antihypertensive activity of timolol is maintained with long-term therapy and is well tolerated.

The mechanism of the antihypertensive effects of beta-adrenergic receptor blocking agents is not established at this time. Possible mechanisms of action include reduction in cardiac output, reduction in plasma renin activity, and a central nervous system sympatholytic action.

A Norwegian multi-center, double-blind study, which included patients 20 to 75 years of age, compared the effects of timolol maleate with placebo in 1,884 patients who had survived the acute phase of a myocardial infarction. Patients with systolic blood pressure below 100 mm Hg, sick sinus syndrome and contraindications to beta-blockers, including uncontrolled heart failure, second- or third-degree AV block and bradycardia (< 50 beats per minute), were excluded from the multi-center trial. Therapy with timolol, begun 7 to 28 days following infarction, was shown to reduce overall mortality; this was primarily attributable to a reduction in cardiovascular mortality. Timolol significantly reduced the incidence of sudden deaths (deaths occurring without symptoms or within 24 hours of the onset of symptoms), including those occurring within one hour, and particularly instantaneous deaths (those occurring without preceding symptoms). The protective effect of timolol was consistent regardless of age, sex or site of infarction. The effect was clearest in patients with a first infarction who were considered at a high risk of dying, defined as those with one or more of the following characteristics during the acute phase: transient left ventricular failure, cardiomegaly, newly appearing atrial fibrillation or flutter, systolic hypotension, or SGOT (ASAT) levels greater than four times the upper limit of normal. Therapy with timolol also reduced the incidence of nonfatal reinfarction. The mechanism of the protective effect of timolol is unknown.

Timolol was studied for the prophylactic treatment of migraine headache in placebo-controlled clinical trials involving 400 patients, mostly women between the ages of 18 and 66 years. Common migraine was the most frequent diagnosis. All patients had at least two headaches per month at baseline. Approximately 50 percent of patients who received timolol had a reduction in the frequency of migraine headache of at least 50 percent, compared to a similar decrease in frequency in 30 percent of patients receiving placebo. The most common cardiovascular adverse effect was bradycardia (5%).

Pharmacokinetics and Metabolism

Timolol maleate is rapidly and nearly completely absorbed (about 90%) following oral ingestion. Detectable plasma levels of timolol occur within one-half hour and peak plasma levels occur in about one to two hours. The drug half-life in plasma is approximately 4 hours and this is essentially unchanged in patients with moderate renal insufficiency. Timolol is partially metabolized by the liver and timolol and its metabolites are excreted by the kidney. Timolol is not extensively bound to plasma proteins; i.e., < 10% by equilibrium dialysis and approximately 60% by ultrafiltration. An in vitro hemodialysis study, using ^14C timolol added to human plasma or whole blood, showed that timolol was readily dialyzed from these fluids; however, a study of patients with renal failure showed that timolol did not dialyze readily. Plasma levels following oral administration are about half those following intravenous administration indicating approximately 50% first pass metabolism. The level of beta sympathetic activity varies widely among individuals, and no simple correlation exists between the dose or plasma level of timolol maleate and its therapeutic activity. Therefore, objective clinical measurements such as reduction of heart rate and/or blood pressure should be used as guides in determining the optimal dosage for each patient.

INDICATIONS AND USAGE

Hypertension

Timolol maleate tablets are indicated for the treatment of hypertension. They may be used alone or in combination with other antihypertensive agents, especially thiazide-type diuretics.

Myocardial Infarction

Timolol is indicated in patients who have survived the acute phase of myocardial infarction, and are clinically stable, to reduce cardiovascular mortality and the risk of reinfarction.

Migraine

Timolol is indicated for the prophylaxis of migraine headache.

CONTRAINDICATIONS

Timolol maleate is contraindicated in patients with bronchial asthma or with a history of bronchial asthma, or severe chronic obstructive pulmonary disease (see WARNINGS); sinus bradycardia; second- and third-degree atrioventricular block; overt cardiac failure (see WARNINGS); cardiogenic shock; hypersensitivity to this product.

WARNINGS

Cardiac Failure

Sympathetic stimulation may be essential for support of the circulation in individuals with diminished myocardial contractility, and its inhibition by beta-adrenergic receptor blockade may precipitate more severe failure. Although beta-blockers should be avoided in overt congestive heart failure, they can be used, if necessary, with caution in patients with a history of failure who are well compensated, usually with digitalis and diuretics. Both digitalis and timolol maleate slow AV conduction. If cardiac failure persists, therapy with timolol maleate should be withdrawn.

In Patients Without a History of Cardiac Failure

Continued depression of the myocardium with beta-blocking agents over a period of time can, in some cases, lead to cardiac failure. At the first sign or symptom of cardiac failure, patients receiving timolol should be digitalized and/or be given a diuretic, and the response observed closely. If cardiac failure continues, despite adequate digitalization and diuretic therapy, timolol should be withdrawn.

Exacerbation of Ischemic Heart Disease Following Abrupt Withdrawal

Hypersensitivity to catecholamines has been observed in patients withdrawn from beta-blocker therapy; exacerbation of angina and, in some cases, myocardial infarction have occurred after abrupt discontinuation of such therapy. When discontinuing chronically administered timolol maleate, particularly in patients with ischemic heart disease, the dosage should be gradually reduced over a period of one to two weeks and the patient should be carefully monitored. If angina markedly worsens or acute coronary insufficiency develops, timolol maleate administration should be reinstituted promptly, at least temporarily, and other measures appropriate for the management of unstable angina should be taken. Patients should be warned against interruption or discontinuation of therapy without the physician's advice. Because coronary artery disease is common and may be unrecognized, it may be prudent not to discontinue timolol maleate therapy abruptly even in patients treated only for hypertension.

Obstructive Pulmonary Disease

PATIENTS WITH CHRONIC OBSTRUCTIVE PULMONARY DISEASE (e.g., CHRONIC BRONCHITIS, EMPHYSEMA) OF MILD OR MODERATE SEVERITY, BRONCHOSPASTIC DISEASE OR A HISTORY OF BRONCHOSPASTIC DISEASE (OTHER THAN BRONCHIAL ASTHMA OR A HISTORY OF BRONCHIAL ASTHMA, IN WHICH 'TIMOLOL MALEATE' IS CONTRAINDICATED, see CONTRAINDICATIONS), SHOULD IN GENERAL NOT RECEIVE BETA-BLOCKERS, INCLUDING 'TIMOLOL'. However, if timolol is necessary in such patients, then the drug should be administered with caution since it may block bronchodilation produced by endogenous and exogenous catecholamine stimulation of beta2 receptors.

Major Surgery

The necessity or desirability of withdrawal of beta-blocking therapy prior to major surgery is controversial. Beta-adrenergic receptor blockade impairs the ability of the heart to respond to beta-adrenergically mediated reflex stimuli. This may augment the risk of general anesthesia in surgical procedures. Some patients receiving beta-adrenergic receptor blocking agents have been subject to protracted severe hypotension during anesthesia. Difficulty in restarting and maintaining the heartbeat has also been reported. For these reasons, in patients undergoing elective surgery, some authorities recommend gradual withdrawal of beta-adrenergic receptor blocking agents.

If necessary during surgery, the effects of beta-adrenergic blocking agents may be reversed by sufficient doses of such agonists as isoproterenol, dopamine, dobutamine or norepinephrine (see OVERDOSAGE).

Diabetes Mellitus

Timolol should be administered with caution in patients subject to spontaneous hypoglycemia or to diabetic patients (especially those with labile diabetes) who are receiving insulin or oral hypoglycemic agents. Beta-adrenergic receptor blocking agents may mask the signs and symptoms of acute hypoglycemia.

Thyrotoxicosis

Beta-adrenergic blockade may mask certain clinical signs (e.g., tachycardia) of hyperthyroidism. Patients suspected of developing thyrotoxicosis should be managed carefully to avoid abrupt withdrawal of beta-blockade which might precipitate a thyroid storm.

PRECAUTIONS

General

Impaired Hepatic or Renal Function

Since timolol is partially metabolized in the liver and excreted mainly by the kidneys, dosage reductions may be necessary when hepatic and/or renal insufficiency is present.

Dosing in the Presence of Marked Renal Failure

Although the pharmacokinetics of timolol are not greatly altered by renal impairment, marked hypotensive responses have been seen in patients with marked renal impairment undergoing dialysis after 20 mg doses. Dosing in such patients should therefore be especially cautious.

Muscle Weakness

Beta-adrenergic blockade has been reported to potentiate muscle weakness consistent with certain myasthenic symptoms (e.g., diplopia, ptosis, and generalized weakness). Timolol has been reported rarely to increase muscle weakness in some patients with myasthenia gravis or myasthenic symptoms.

Cerebrovascular Insufficiency

Because of potential effects of beta-adrenergic blocking agents relative to blood pressure and pulse, these agents should be used with caution in patients with cerebrovascular insufficiency. If signs or symptoms suggesting reduced cerebral blood flow are observed, consideration should be given to discontinuing these agents.

Drug Interactions

Catecholamine-Depleting Drugs

Close observation of the patient is recommended when timolol is administered to patients receiving catecholamine-depleting drugs such as reserpine, because of possible additive effects and the production of hypotension and/or marked bradycardia, which may produce vertigo, syncope, or postural hypotension.

Non-Steroidal Anti-Inflammatory Drugs

Blunting of the antihypertensive effect of beta-adrenoceptor blocking agents by non-steroidal anti-inflammatory drugs has been reported. When using these agents concomitantly, patients should be observed carefully to confirm that the desired therapeutic effect has been obtained.

Calcium Antagonists

Literature reports suggest that oral calcium antagonists may be used in combination with beta-adrenergic blocking agents when heart function is normal, but should be avoided in patients with impaired cardiac function. Hypotension, AV conduction disturbances, and left ventricular failure have been reported in some patients receiving beta-adrenergic blocking agents when an oral calcium antagonist was added to the treatment regimen. Hypotension was more likely to occur if the calcium antagonist were a dihydropyridine derivative, e.g., nifedipine, while left ventricular failure and AV conduction disturbances were more likely to occur with either verapamil or diltiazem.

Intravenous calcium antagonists should be used with caution in patients receiving beta-adrenergic blocking agents.

Digitalis and Either Diltiazem or Verapamil

The concomitant use of beta-adrenergic blocking agents with digitalis and either diltiazem or verapamil may have additive effects in prolonging AV conduction time.

Quinidine

Potentiated systemic beta-blockade (e.g., decreased heart rate) has been reported during combined treatment with quinidine and timolol, possibly because quinidine inhibits the metabolism of timolol via the P-450 enzyme, CYP2D6.

Clonidine

Beta-adrenergic blocking agents may exacerbate the rebound hypertension which can follow the withdrawal of clonidine. If the two drugs are coadministered, the beta-adrenergic blocking agent should be withdrawn several days before the gradual withdrawal of clonidine. If replacing clonidine by beta-blocker therapy, the introduction of beta-adrenergic blocking agents should be delayed for several days after clonidine administration has stopped.

Risk from Anaphylactic Reaction

While taking beta-blockers, patients with a history of atopy or a history of severe anaphylactic reaction to a variety of allergens may be more reactive to repeated accidental, diagnostic, or therapeutic challenge with such allergens. Such patients may be unresponsive to the usual doses of epinephrine used to treat anaphylactic reactions.

Carcinogenesis, Mutagenesis, Impairment of Fertility

In a 2 year study of timolol maleate in rats, there was a statistically significant increase in the incidence of adrenal pheochromocytomas in male rats administered 300 mg/kg/day (250 times^1 the maximum recommended human dose). Similar differences were not observed in rats administered doses equivalent to approximately 20 or 80 times^1 the maximum recommended human dose.

In a lifetime study in mice, there were statistically significant increases in the incidence of benign and malignant pulmonary tumors, benign uterine polyps and mammary adenocarcinoma in female mice at 500 mg/kg/day (approximately 400 times^1 the maximum recommended human dose), but not at a 5 or 50 mg/kg/day. In a subsequent study in female mice, in which postmortem examinations were limited to uterus and lungs, a statistically significant increase in the incidence of pulmonary tumors was again observed at 500 mg/kg/day.

The increased occurrence of mammary adenocarcinoma was associated with elevations in serum prolactin that occurred in female mice administered timolol maleate at 500 mg/kg/day, but not at doses of 5 or 50 mg/kg/day. An increased incidence of mammary adenocarcinomas in rodents has been associated with administration of several other therapeutic agents which elevate serum prolactin, but no correlation between serum prolactin levels and mammary tumors has been established in man. Furthermore, in adult human female subjects who received oral dosages of up to 60 mg of timolol maleate, the maximum recommended daily human oral dosage, there were no clinically meaningful changes in serum prolactin.

Timolol maleate was devoid of mutagenic potential when evaluated in vivo (mouse) in the micronucleus test and cytogenetic assay (doses up to 800 mg/kg) and in vitro in a neoplastic cell transformation assay (up to 100 mcg/mL). In Ames tests the highest concentrations of timolol employed, 5,000 or 10,000 mcg/plate, were associated with statistically significant elevations of revertants observed with tester strain TA100 (in seven replicate assays), but not in three additional strains. In the assays with tester strain TA100, no consistent dose-response relationship was observed, nor did the ratio of test to control revertants reach 2. A ratio of 2 is usually considered the criterion for a positive Ames test.

Reproduction and fertility studies in rats showed no adverse effect on male or female fertility at doses up to 125 times^1 the maximum recommended human dose.

^1Based on patient weight of 50 kg.

Pregnancy

Teratogenic Effects

Teratogenicity studies with timolol in mice, rats and rabbits at doses up to 50 mg/kg/day (approximately 40 times^1 the maximum recommended daily human dose) showed no evidence of fetal malformations. Although delayed fetal ossification was observed at this dose in rats, there were no adverse effects on postnatal development of offspring. Doses of 1000 mg/kg/day (approximately 830 times^1 the maximum recommended daily human dose) were maternotoxic in mice and resulted in an increased number of fetal resorptions. Increased fetal resorptions were also seen in rabbits at doses of approximately 40 times^1 the maximum recommended daily human dose, in this case without apparent maternotoxicity. There are no adequate and well controlled studies in pregnant women. Timolol should be used during pregnancy only if the potential benefit justifies the potential risk to the fetus.

Nursing Mothers

Timolol maleate has been detected in human milk.

Because of the potential for serious adverse reactions from timolol in nursing infants, a decision should be made whether to discontinue nursing or to discontinue the drug, taking into account the importance of the drug to the mother.

Pediatric Use

Safety and effectiveness in pediatric patients have not been established.

Geriatric Use

Clinical studies of timolol for the treatment of hypertension or migraine did not include sufficient numbers of subjects aged 65 and over to determine whether they respond differently from younger subjects.

In a clinical study of timolol in patients who had survived the acute phase of a myocardial infarction, approximately 350 patients (37%) were 65 to 75 years of age. Safety and efficacy were not different between these patients and younger patients (see CLINICAL PHARMACOLOGY: Pharmacodynamics).

Other reported clinical experience has not identified differences in response between the elderly and younger patients. In general, dose selection for an elderly patient should be cautious, usually starting at the low end of the dosing range, reflecting the greater frequency of decreased hepatic, renal or cardiac function, and of concomitant disease or other drug therapy.

This drug is known to be substantially excreted by the kidney, and the risk of toxic reactions to this drug may be greater in patients with impaired renal function. Because elderly patients are more likely to have decreased renal function, care should be taken in dose selection, and it may be useful to monitor renal function. (See PRECAUTIONS: Impaired Hepatic or Renal Function and Dosing in the Presence of Marked Renal Failure.)

ADVERSE REACTIONS

Timolol maleate tablets are usually well tolerated in properly selected patients. Most adverse effects have been mild and transient.

In a multi-center (12 week) clinical trial comparing timolol maleate and placebo in hypertensive patients, the following adverse reactions were reported spontaneously and considered to be causally related to timolol maleate:

 | Timolol Maleate (n=176) % | Placebo (n=168) %
BODY AS A WHOLE
fatigue/tiredness | 3.4 | 0.6
headache | 1.7 | 1.8
chest pain | 0.6 | 0
asthenia | 0.6 | 0
CARDIOVASCULAR
bradycardia | 9.1 | 0
arrhythmia | 1.1 | 0.6
syncope | 0.6 | 0
edema | 0.6 | 1.2
DIGESTIVE
dyspepsia | 0.6 | 0.6
nausea | 0.6 | 0
SKIN
pruritus | 1.1 | 0
NERVOUS SYSTEM
dizziness | 2.3 | 1.2
vertigo | 0.6 | 0
paresthesia | 0.6 | 0
PSYCHIATRIC
decreased libido | 0.6 | 0
RESPIRATORY
dyspnea | 1.7 | 0.6
bronchial spasm | 0.6 | 0
rales | 0.6 | 0
SPECIAL SENSES
eye irritation | 1.1 | 0.6
tinnitus | 0.6 | 0

These data are representative of the incidence of adverse effects that may be observed in properly selected patients treated with timolol maleate, i.e., excluding patients with bronchospastic disease, congestive heart failure or other contraindications to beta-blocker therapy.

In patients with migraine the incidence of bradycardia was 5 percent.

In a coronary artery disease population studied in the Norwegian multi-center trial (see CLINICAL PHARMACOLOGY), the frequency of the principal adverse reactions and the frequency with which these resulted in discontinuation of therapy in the timolol and placebo groups were:

 | Adverse Reaction* |  | Withdrawal†
 | Timolol (n=945) % | Placebo (n=939) % | Timolol (n=945) % | Placebo (n=939) %
Asthenia or Fatigue | 5 | 1 | <1 | <1
Heart Rate < 40 beats/minute | 5 | <1 | 4 | <1
Cardiac Failure-Nonfatal | 8 | 7 | 3 | 2
Hypotension | 3 | 2 | 3 | 1
Pulmonary Edema-Nonfatal | 2 | <1 | <1 | <1
Claudication | 3 | 3 | 1 | <1
AV Block 2nd or 3rd Degree | <1 | <1 | <1 | <1
Sinoatrial Block | <1 | <1 | <1 | <1
Cold Hands and Feet | 8 | <1 | <1 | 0
Nausea or Digestive Disorders | 8 | 6 | 1 | <1
Dizziness | 6 | 4 | 1 | 0
Bronchial Obstruction | 2 | <1 | 1 | <1

*When an adverse reaction recurred in a patient, it is listed only once.

†Only principal reason for withdrawal in each patient is listed. These adverse reactions can also occur in patients treated for hypertension.

The following additional adverse effects have been reported in clinical experience with the drug: Body as a Whole: anaphylaxis, extremity pain, decreased exercise tolerance, weight loss, fever; Cardiovascular: cardiac arrest, cardiac failure, cerebral vascular accident, worsening of angina pectoris, worsening of arterial insufficiency, Raynaud's phenomenon, palpitations, vasodilatation; Digestive:gastrointestinal pain, hepatomegaly, vomiting, diarrhea, dyspepsia; Hematologic:nonthrombocytopenic purpura; Endocrine:hyperglycemia, hypoglycemia; Skin: rash, skin irritation, increased pigmentation, sweating, alopecia; Musculoskeletal: arthralgia; Nervous System: local weakness, increase in signs and symptoms of myasthenia gravis; Psychiatric: depression, nightmares, somnolence, insomnia, nervousness, diminished concentration, hallucinations; Respiratory:cough; Special Senses: visual disturbances, diplopia, ptosis, dry eyes; Urogenital: impotence, urination difficulties.

There have been reports of retroperitoneal fibrosis in patients receiving timolol maleate and in patients receiving other beta-adrenergic blocking agents. A causal relationship between this condition and therapy with beta-adrenergic blocking agents has not been established.

Potential Adverse Effects

In addition, a variety of adverse effects not observed in clinical trials with timolol maleate, but reported with other beta-adrenergic blocking agents, should be considered potential adverse effects of timolol. Nervous System: Reversible mental depression progressing to catatonia; an acute reversible syndrome characterized by disorientation for time and place, short-term memory loss, emotional lability, slightly clouded sensorium, and decreased performance on neuropsychometrics; Cardiovascular: Intensification of AV block (see CONTRAINDICATIONS); Digestive: Mesenteric arterial thrombosis, ischemic colitis; Hematologic: Agranulocytosis, thrombocytopenic purpura; Allergic: Erythematous rash, fever combined with aching and sore throat, laryngospasm with respiratory distress; Miscellaneous: Peyronie's disease.

There have been reports of a syndrome comprising psoriasiform skin rash, conjunctivitis sicca, otitis, and sclerosing serositis attributed to the beta-adrenergic receptor blocking agent, practolol. This syndrome has not been reported with timolol.

Clinical Laboratory Test Findings

Clinically important changes in standard laboratory parameters were rarely associated with the administration of timolol. Slight increases in blood urea nitrogen, serum potassium, uric acid, and triglycerides, and slight decreases in hemoglobin, hematocrit and HDL cholesterol occurred, but were not progressive or associated with clinical manifestations. Increases in liver function tests have been reported.

To report SUSPECTED ADVERSE REACTIONS, contact Rising Pharma Holdings, Inc. at 1-844-874-7464 or FDA at 1-800-FDA-1088 or www.fda. gov/medwatch.

OVERDOSAGE

Overdosage has been reported with timolol maleate tablets. A 30 year old female ingested 650 mg of timolol maleate (maximum recommended daily dose - 60 mg) and experienced second- and third-degree heart block. She recovered without treatment but approximately 2 months later developed irregular heart beat, hypertension, dizziness, tinnitus, faintness, increased pulse rate and borderline first degree heart block.

The oral LD50 of the drug is 1190 and 900 mg/kg in female mice and female rats, respectively.

An in vitro hemodialysis study, using ^14C timolol added to human plasma or whole blood, showed that timolol was readily dialyzed from these fluids; however, a study of patients with renal failure showed that timolol did not dialyze readily.

The most common signs and symptoms to be expected with overdosage with a beta-adrenergic receptor blocking agent are symptomatic bradycardia, hypotension, bronchospasm, and acute cardiac failure. Therapy with timolol should be discontinued and the patient observed closely. The following additional therapeutic measures should be considered:

• (1) Gastric lavage

• (2) Symptomatic bradycardia: Use atropine sulfate intravenously in a dosage of 0.25 mg to 2 mg to induce vagal blockade. If bradycardia persists, intravenous isoproterenol hydrochloride should be administered cautiously. In refractory cases the use of a transvenous cardiac pacemaker may be considered.

• (3) Hypotension: Use sympathomimetic pressor drug therapy, such as dopamine, dobutamine or norepinephrine. In refractory cases the use of glucagon hydrochloride has been reported to be useful.

• (4) Bronchospasm: Use isoproterenol hydrochloride. Additional therapy with aminophylline may be considered.

• (5) Acute cardiac failure: Conventional therapy with digitalis, diuretics, and oxygen should be instituted immediately. In refractory cases the use of intravenous aminophylline is suggested. This may be followed if necessary by glucagon hydrochloride which has been reported to be useful.

• (6) Heart block (second- or third-degree): Use isoproterenol hydrochloride or a transvenous cardiac pacemaker.

DOSAGE AND ADMINISTRATION

Hypertension

The usual initial dosage of timolol maleate is 10 mg twice a day, whether used alone or added to diuretic therapy. Dosage may be increased or decreased depending on heart rate and blood pressure response. The usual total maintenance dosage is 20 to 40 mg per day. Increases in dosage to a maximum of 60 mg per day divided into two doses may be necessary. There should be an interval of at least 7 days between increases in dosages.

Timolol maleate tablets may be used with a thiazide diuretic or with other antihypertensive agents. Patients should be observed carefully during initiation of such concomitant therapy.

Myocardial Infarction

The recommended dosage for long-term prophylactic use in patients who have survived the acute phase of a myocardial infarction is 10 mg given twice daily (see CLINICAL PHARMACOLOGY).

Migraine

The usual initial dosage of timolol maleate is 10 mg twice a day. During maintenance therapy the 20 mg daily dosage may be administered as a single dose. Total daily dosage may be increased to a maximum of 30 mg, given in divided doses, or decreased to 10 mg once per day, depending on clinical response and tolerability. If a satisfactory response is not obtained after 6 to 8 weeks use of the maximum daily dosage, therapy with timolol should be discontinued.

HOW SUPPLIED

Timolol Maleate Tablets, USP are available containing 5 mg, 10 mg and 20 mg of timolol maleate, USP.

The 5 mg tablet is white to off white round tablet, engraved IT70 on one side and the other side is plain. They are available as follows:

NDC 16571-223-01
bottles of 100 tablets

The 10 mg tablet is white to off white round tablet, engraved IT above bisect and 71 below bisect on one side and other side is plain. They are available as follows:

NDC 16571-224-01
bottles of 100 tablets

The 20 mg tablet is white to off white, capsule shaped tablet, engraved IT bisect 72 on one side and other side is plain. They are available as follows:

NDC 16571-225-01
bottles of 100 tablets

Store at 20° to 25°C (68° to 77°F). [See USP for Controlled Room Temperature.]

Protect from light.

Dispense in a tight, light-resistant container as defined in the USP using a child-resistant closure.

Keep container tightly closed.

Manufactured for:
Rising Pharma Holdings, Inc.
East Brunswick, NJ 08816

Issued: 05/2024

PIR22501-00

PRINCIPAL DISPLAY PANEL

Timolol Maleate Tablets, USP 5mg

100 Tablets Bottle Label

Timolol Maleate Tablets, USP 10mg

100 Tablets Bottle Label

Timolol Maleate Tablets, USP 20mg

100 Tablets Bottle Label